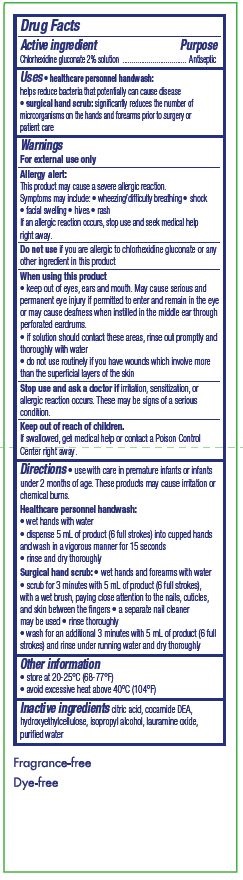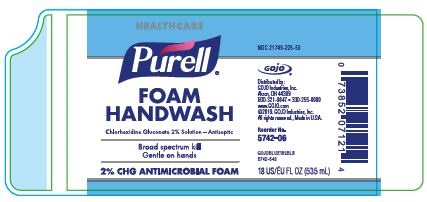 DRUG LABEL: Purell Antimicrobial Foam
NDC: 21749-225 | Form: LIQUID
Manufacturer: GOJO Industries, Inc.
Category: otc | Type: HUMAN OTC DRUG LABEL
Date: 20190618

ACTIVE INGREDIENTS: CHLORHEXIDINE GLUCONATE 20 mg/1 mL
INACTIVE INGREDIENTS: HYDROXYETHYL CELLULOSE (2000 CPS AT 1%); WATER; LAURAMINE OXIDE; CITRIC ACID MONOHYDRATE; COCO DIETHANOLAMIDE; ISOPROPYL ALCOHOL

Purell Foam Handwash

Drug Facts

Active ingredient

Chlorhexidine Gluconate 2% Solution

Purpose

Antiseptic

Uses

healthcare personnel handwash:

helps reduce bacteria that potentially can cause disease

surgical hand scrub:

significantly reduces the number of microorganisms on the hands and forearms prior to surgery or patient care

Warnings

For external use only

Allergy alert:

This product may cause a severe allergic reaction. Symptoms may include:

wheezing/difficulty breathing

shock

facial swelling

hives

rash

If an allergy reaction occurs, stop use and seek madical help right away.

Do not use

If you are allerigic to chlorhexidine gluconate or any other ingredient in this product

When using this product

keep out of eyes, ears, and mouth. May cause serious and permanent eye injury if permitted to enter and remain in the eye or may cause deafness when instilled in the middle ear through perforated eardrums.

If solution should contact these areas, rinse out promptly and thoroughly with water

Do not use routinely if you have wounds which invlove more than the superficial layers of the skin

Stop use and ask doctor if

irritation, sensitization, or allerigic reaction occurs. These may be signs of a serious condition.

Keep out of reach of children.

If swallowed, get medical help or contact a Poison Control Center right away.

Directions

use with care in premature infants or infants under two months of age. These products may cuase irritation or chemical burns

Healthcare personnel handwash:

wet hands with water

dispense 5 mL of product (6 full strokes) into cupped hands and wash in a vigorous manner for 15 seconds

rinse and dry thoroughly

Surgical hand scrub

wet hands and forearms with water

scrub for 3 minutes with 5 mL of product (6 full strokes), with a wet brush, paying close attention to the nails, cuticles, and skin between the fingers

a seperate nail cleaner may be used

rinse thoroughly

wash for an additional 3 minutes with 5 mL of product (6 full strokes) and rinse under running water and dry thoroughly

Other information

store at 20-25ºC (68-77ºF)

avoid excessive heat above 40ºC (104ºF)

Inactive ingredients

citric acid, cocamide DEA, hydroxyethylcellulose, isopropyl alcohol, lauramine oxide, purified water

PACKAGE LABEL

NDC 21749-225-53

Purell

FOAM HANDWASH

Chlorhexidine Gluconate 2% Solution - Antiseptic

Broad spectrum kill

Gentle on hands

2% CHG ANTIMICROBIAL FOAM

Distributed by:

GOJO Industries, Inc.

Akron, OH 44309

800-321-9647 • 330-255-6000

www.GOJO.com

©2019. GOJO Industries, Inc.

All rights reserved., Made in U.S.A.

Reorder 5742-06

GOJOBLUE18LBLB

5742-643